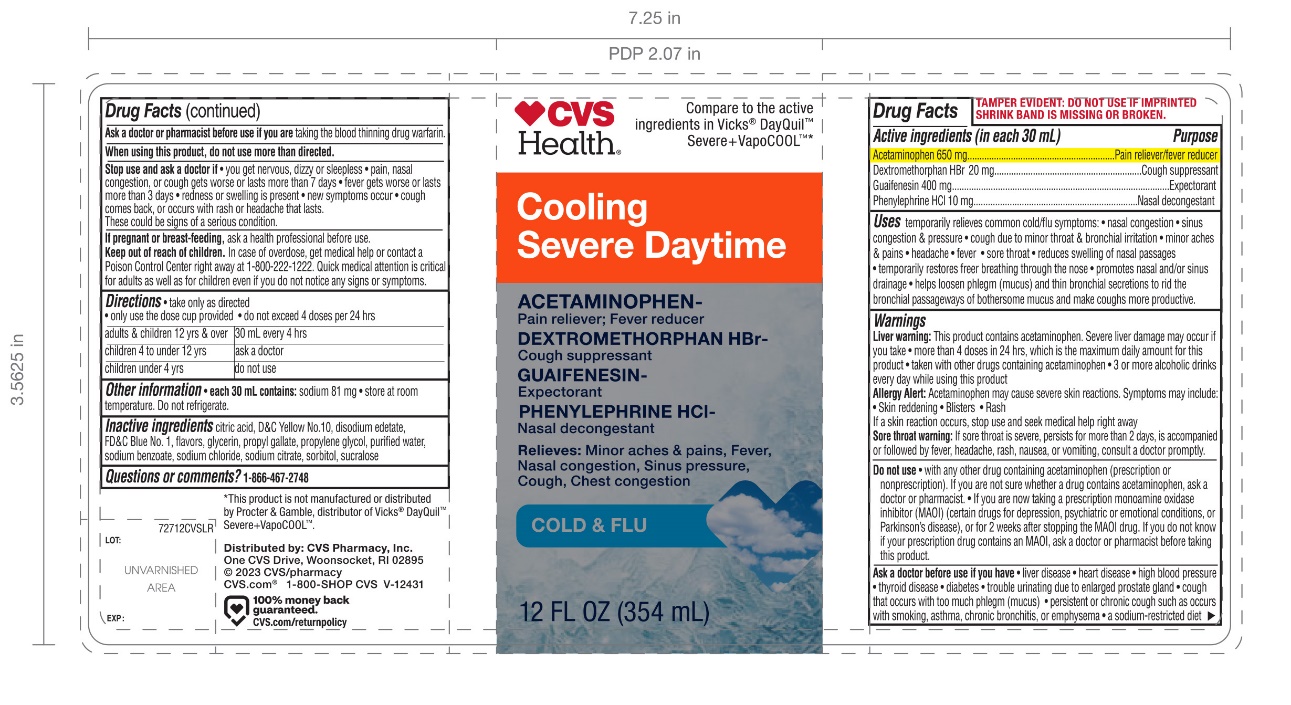 DRUG LABEL: CVS Daytime Cold and Flu Relief
NDC: 51316-727 | Form: LIQUID
Manufacturer: CVS PHARMACY
Category: otc | Type: HUMAN OTC DRUG LABEL
Date: 20251209

ACTIVE INGREDIENTS: ACETAMINOPHEN 650 mg/30 mL; DEXTROMETHORPHAN HYDROBROMIDE 20 mg/30 mL; GUAIFENESIN 400 mg/30 mL; PHENYLEPHRINE HYDROCHLORIDE 10 mg/30 mL
INACTIVE INGREDIENTS: ANHYDROUS CITRIC ACID; D&C YELLOW NO. 10; EDETATE DISODIUM; FD&C BLUE NO. 1; GLYCERIN; PROPYL GALLATE; PROPYLENE GLYCOL; WATER; SODIUM BENZOATE; SODIUM CHLORIDE; SODIUM CITRATE, UNSPECIFIED FORM; SORBITOL; SUCRALOSE

CVS DayTime Severe Cooling Cold and Flu Relief

Active ingredients (in each 30 mL)

Acetaminophen 650 mg

Dextromethorphan HBr 20 mg

Guaifenesin 400 mg

Phenylephrine HCl 10 mg

Purposes

Pain reliever/fever reducer

Cough suppressant

Expectorant

Nasal decongestant

Uses

- temporarily relieves common cold/flu symptoms:
  - nasal congestion
  - sinus congestion & pressure
  - cough due to minor throat and bronchial irritation
  - minor aches and pains
  - headache
  - fever
  - sore throat
  - reduce swelling of nasal passages
  - temporarily restores freer breathing through the nose
  - promotes nasal and/or sinus drainage
- help loosen phlegm (mucus) and thin bronchial secretions to rid the bronchial passageways of bothersome mucus and make cough more productive

Warnings

Liver warning:This product contains acetaminophen. Severe liver damage may occur if you take:

- more than 4 doses in 24 hrs which is maximum daily amount for this product
- taken with other drugs containing acetaminophen
- 3 or more alcoholic drinks every day while using this product

Allergy alert: Acetaminophen may cause severe skin reactions. Symptoms may include:

- Skin reddening
- Blisters
- Rash

If a skin reaction occurs, stop use and seek medical help right away.

Sore throat warning:If sore throat is severe, persists for more than 2 days, is accompanied or followed by fever, headache, rash, nausea, or vomiting, consult a doctor promptly.

Do not use

- with any other drug containing acetaminophen (prescription or non-prescription). If you are not sure whether a drug contains acetaminophen, ask a doctor or pharmacist.
- if you are now taking a prescription monoamine oxidase inhibitor (MAOI) (certain drugs for depression, psychiatric or emotional conditions, or Parkinson's disease) or for 2 weeks after stopping the MAOI drug. If you do not know if your prescription drug contains an MAOI, ask a doctor or pharmacist before taking this product.

Ask a doctor before use if you have

- liver disease
- heart disease
- high blood pressure
- thyroid disease
- diabetes
- trouble urinating due to an enlarged prostate gland
- cough that occurs with too much phlegm (mucus)
- persistent or chronic cough such as occurs with smoking, asthma, or emphysema
- a sodium-restricted diet

Ask a doctor or pharmacist before use if you are

taking the blood thinning drug warfarin.

When using this product,

do not use more than directed.

Stop use and ask a doctor if

- you get nervous, dizzy, or sleepless
- pain, nasal congestion or cough gets worse, or lasts more than 7 days
- fever gets worse or lasts more than 3 days
- redness or swelling is present
- new symptoms occur
- cough comes back or occurs with a rash or headache that lasts. These could be signs of a serious condition.

If pregnant or breast-feeding,

ask a health professional before use.

Keep out of reach of children.

In case of overdose, get medical help or contact a Poison Control Center (1-800-222-1222) right away. Quick medical attention is critical for adults as well as for children even if you do not notice any signs or symptoms.

Directions

- take only as directed
- only use the dose cup provided
- do not exceed 4 doses per 24 hours

Adults & children 12 yrs & over | 30 mL every 4 hrs.
Children 4 to under 12 yrs | Ask a doctor
Children under 4 yrs. | Do not use

Other information

- each 30 mL contains: sodium 81 mg
- store at room temperature. Do not refrigerate

Inactive ingredients

citric acid, D&C Yellow No. 10, disodium edetate, FD&C Blue No. 1, flavors, glycerin, propyl gallate, propylene glycol, purified water, sodium benzoate, sodium chloride, sodium citrate, sorbitol, sucralose

Questions or comments?

1-866-467-2748

Principal Display Panel

Compare tothe active ingredients in VICKS® Dayquil™ Severe+ VapoCOOL™ *

NDC 51316-727-12

Day Time

Cold & Flu Relief

Acetaminophen- Pain Reliever/Fever Reducer

Dextromethorphan HBr - Cough Suppressant

Phenylephrine HCI- Nasal decongestant

For Relieves of

- Minor Aches & Pains, Fever
- Nasal congestion & Sinus Pressure
- Cough
- Chest congestion

12 FL OZ (354 mL)

DO NOT USE IF IMPRINTED SHRINK BAND IS MISSING OR BROKEN

Distributed by:

*This product.is not manufactured or distributed by Procter & Gamble, distributer of Vicks® Dayquil™ Severe+ VapoCOOL™.